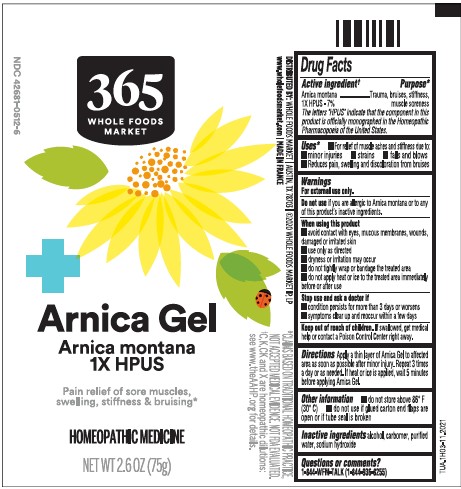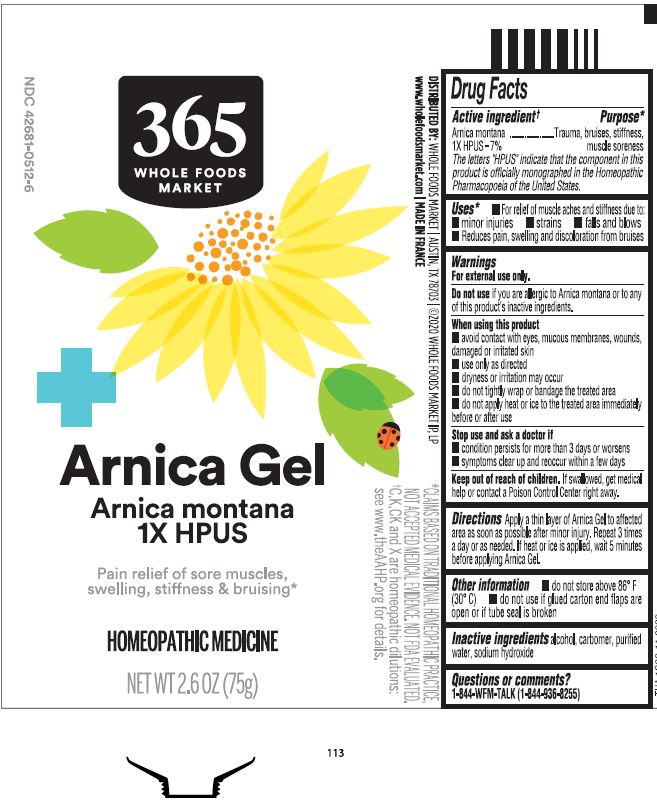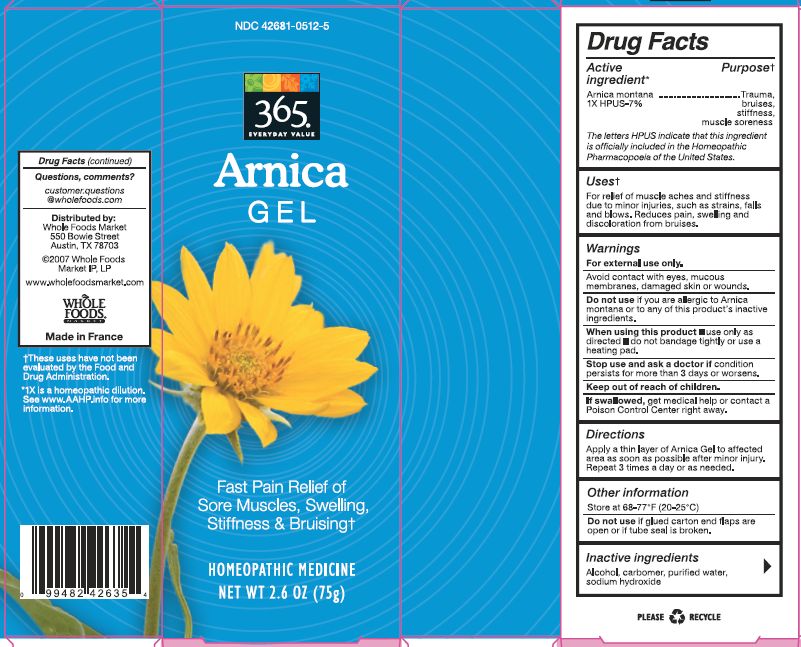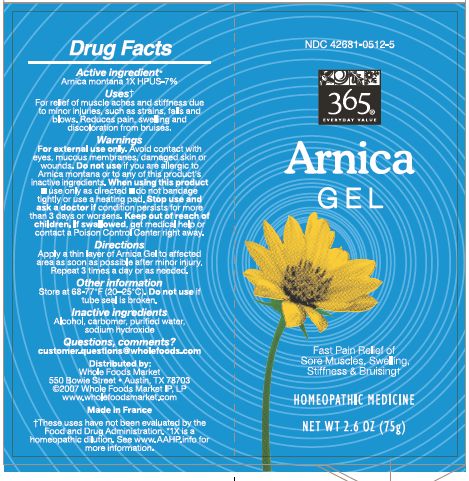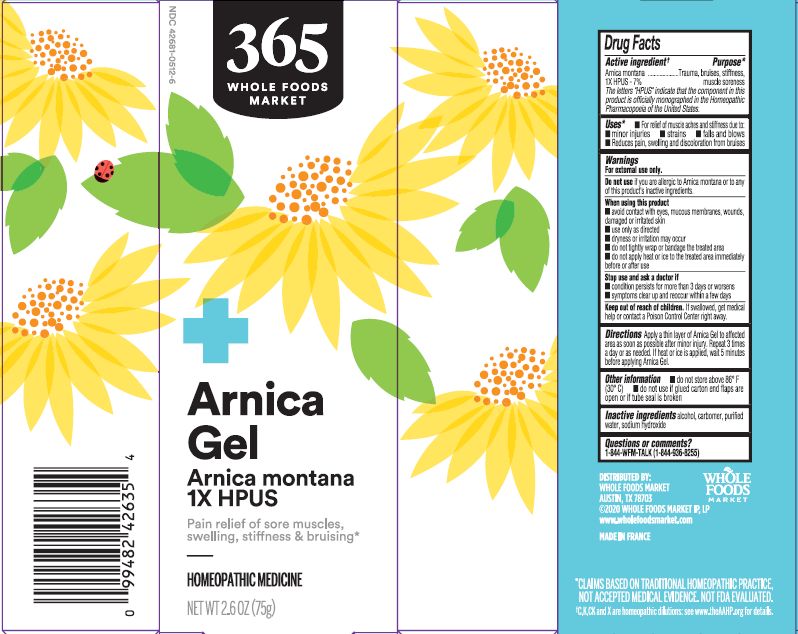 DRUG LABEL: 365 Everyday Value Arnica
NDC: 42681-0512 | Form: GEL
Manufacturer: WFM Private Label, LP
Category: homeopathic | Type: HUMAN OTC DRUG LABEL
Date: 20230718

ACTIVE INGREDIENTS: ARNICA MONTANA 1 [hp_X]/1 1
INACTIVE INGREDIENTS: WATER; ALCOHOL; CARBOMER HOMOPOLYMER TYPE C; SODIUM HYDROXIDE

365 Everyday Value Arnica Gel

Active Ingredient†

Arnica montana 1X HPUS - 7%

The letters "HPUS" indicate that the component in this product is officially monographed in the Homeopathic Pharmacopoeia of the United States.

Purpose*

Arnica montana 1X HPUS - 7% ... Trauma, bruises, stiffness, muscle soreness

Uses*

For relief of muscle aches and stiffness due to:

- minor injuries
- strains
- falls and blows
- Reduces pain, swelling and discoloration from bruises

WARNINGS

For external use only

Do not use if you are allergic to Arnica montana or to any of this product's inactive ingredients.

When using this product

- avoid contact with eyes, mucous membranes, wounds, damaged or irritated skin
- use only as directed
- dryness or irritation may occur
- do not tightly wrap or bandage the treated area
- do not apply heat or ice to the treated area immediately before or after use

Stop use and ask a doctor if

- condition persists for more than 3 days or worsens
- symptoms clear up and reoccur within a few days

Keep out of reach of children. If swallowed, get medical help or contact a Poison Control Center right away.

DOSAGE AND ADMINISTRATION

Directions Apply a thin layer of Arnica Gel to affected area as soon as possible after minor injury. Repeat 3 times a day or as needed. If heat or ice is applied, wait 5 minutes before applying Arnica Gel.

Other information

- do not store above 86° F (30° C)
- do not use if glue carton end flaps are open or if tube seal is broken

INACTIVE INGREDIENT

Inactive ingredients alcohol, carbomer, purified water, sodium hydroxide

Pain relief of sore muscles, swelling, stiffness & bruising*

Homeopathic Medicine

NET WT 2.6 OZ (75g)

*CLAIMS BASED ON TRADITIONAL HOMEOPATHIC PRACTICE, NOT ACCEPTED MEDICAL EVIDENCE. NOT FDA EVALUATED.

†C,K,CK, and X are homeopathic dilutions: see www.theAAHP.org for details

Questions or comments?

1-844-WFM-TALK (1-844-936-8255)

Distributed by:

Whole Foods Market

Austin, TX 78703

© 2020 WHOLE FOODS MARKET IP, LP

www.wholefoodsmarket.com

MADE IN FRANCE